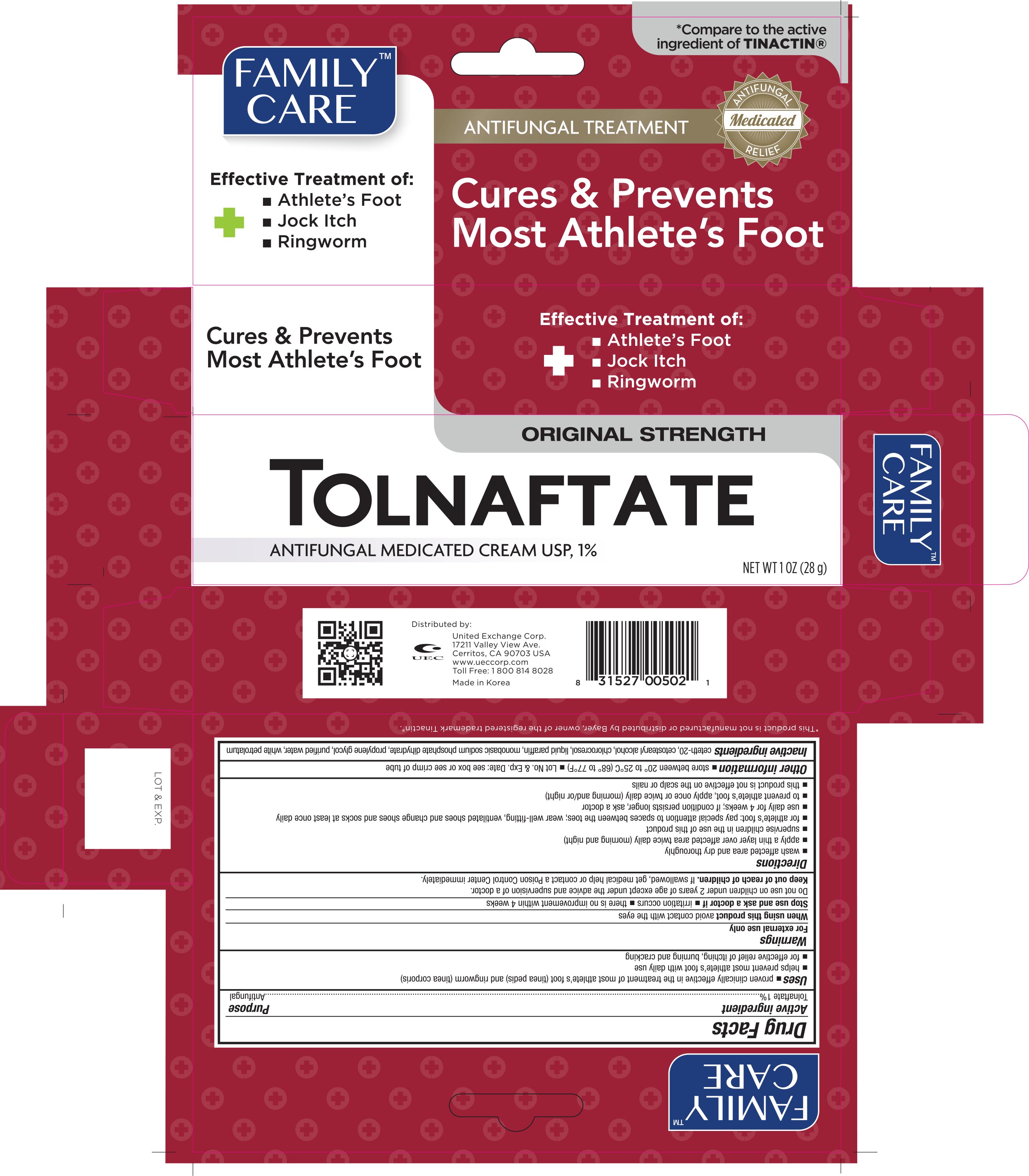 DRUG LABEL: Family Care Tolnaftate

NDC: 65923-502 | Form: CREAM
Manufacturer: United Exchange Corp.
Category: otc | Type: HUMAN OTC DRUG LABEL
Date: 20211222

ACTIVE INGREDIENTS: TOLNAFTATE 10 mg/1 g
INACTIVE INGREDIENTS: CETETH-20; CETOSTEARYL ALCOHOL; CHLOROCRESOL; PARAFFIN; SODIUM PHOSPHATE, MONOBASIC, DIHYDRATE; PROPYLENE GLYCOL; WATER; PETROLATUM

Family Care Tolnaftate Cream 1oz (502 TG, 2018)

Active ingredient Purpose

Tolnaftate 1%........................................................ Antifungal

Uses

- proven clinically effective in the treatment of athlete's foot (tinea pedis) and ringworm (tinea corporis)
- helps prevent most athlete's foot with daily use
- for effective relief of itching, burning and cracking

Warnings

For external use only

When using this product avoid contact with the eyes

Stop use and ask a doctor if

- irritation occurs
- there is no improvement within 4 weeks

Do not use on children under 2 years of age except under the advice and supervision of a doctor

Keep out of reach of children. If swallowed, get medical help or contact a Poison Control Center immediately

Directions

- wash affected area and dry thoroughly
- apply a thin layer over affected area twice daily (morning and night)
- supervise children in the use of this product
- for athlete's foot: pay special attention to spaces between the toes; wear well-fitting, ventilated shoes and change shoes and socks at least once daily
- use daily for 4 weeks; if condition persists longer, ask a doctor
- to prevent athlete's foot, apply once or twice daily (morning and/or night)
- this product is not effective on the scalp or nails

Other information

- store between 20° to 25°C (68° and 77°F)
- Lot No. and Exp. Date: see box or see crimp of tube

INACTIVE INGREDIENT

Inactive ingredients ceteth-20, cetostearyl alcohol, chlorocresol, liquid paraffin, monobasic sodium, phosphate, dihydrate, propylene glycol, purified water, white petrolatum

DOSAGE AND ADMINISTRATION

Distributed By:

United Exchange Corp.

17211 Valley View Ave.

Cerritos, CA 90703 USA

Made in Korea